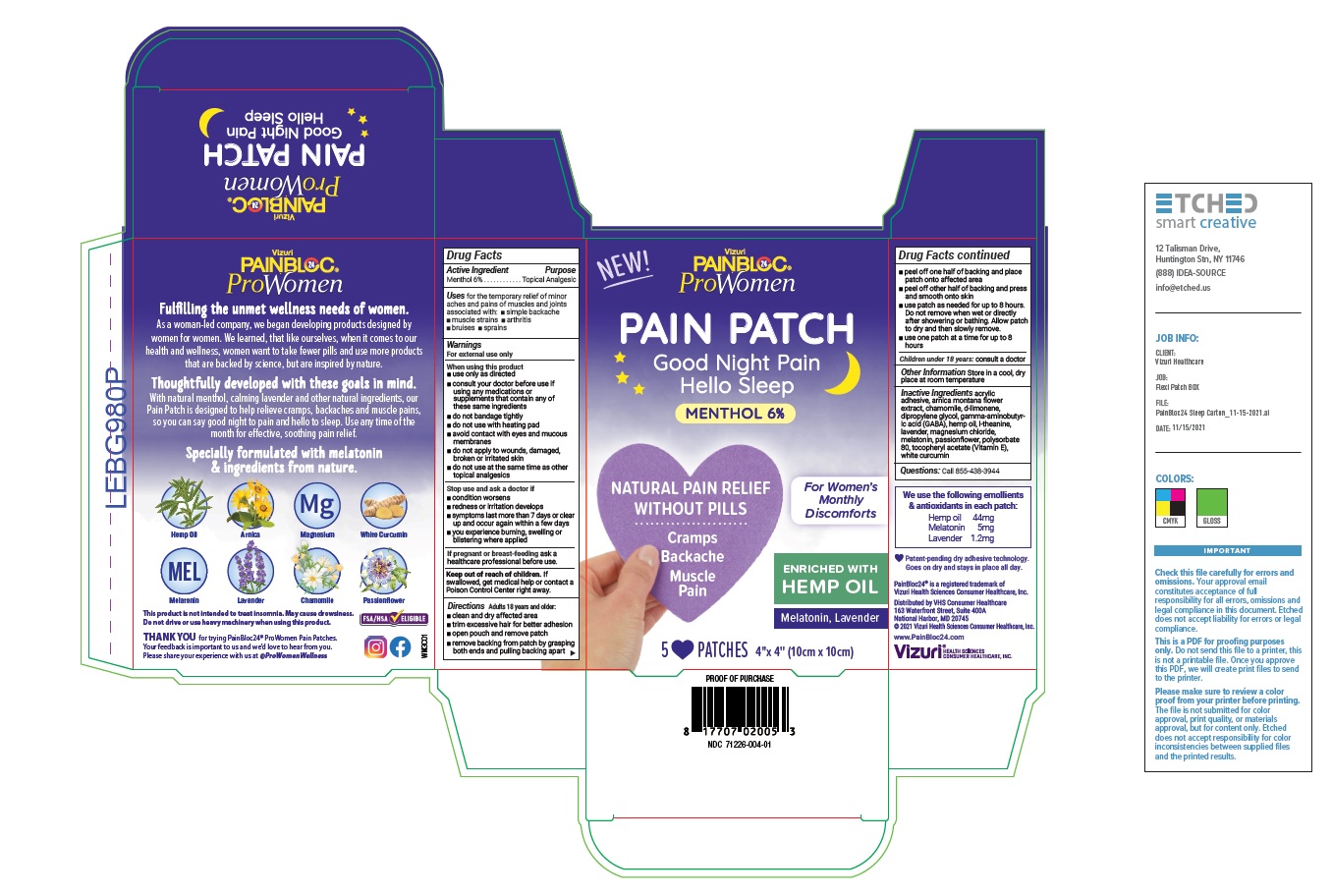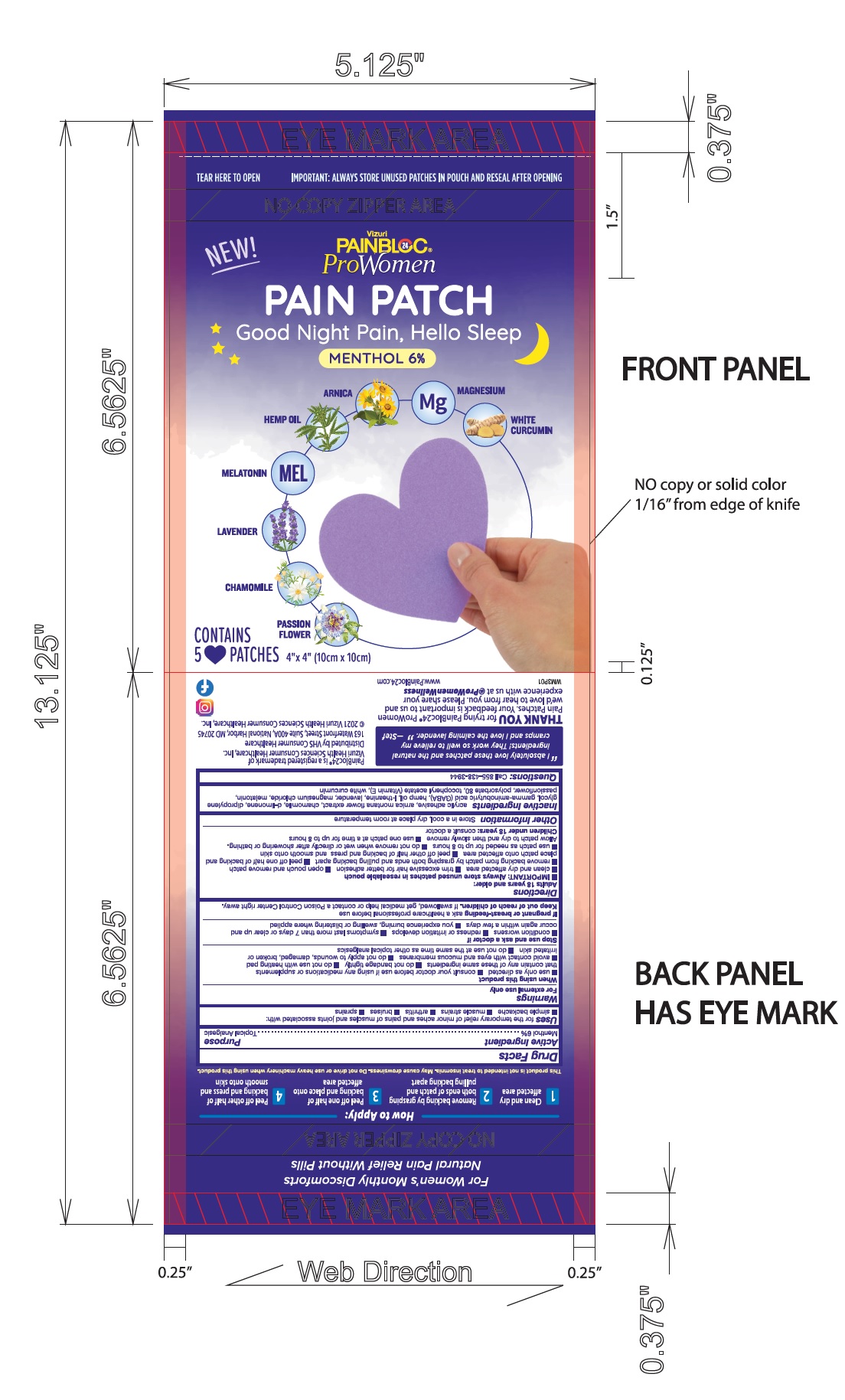 DRUG LABEL: PainBloc24 ProWomen Womens Discomforts Menthol Pain and Sleep Patch
NDC: 71226-004 | Form: PATCH
Manufacturer: VIZURI HEALTH SCIENCES LLC
Category: otc | Type: HUMAN OTC DRUG LABEL
Date: 20220110

ACTIVE INGREDIENTS: MENTHOL 6 g/1 1
INACTIVE INGREDIENTS: ARNICA MONTANA FLOWER; CHAMOMILE; LIMONENE, (+)-; DIPROPYLENE GLYCOL; .GAMMA.-AMINOBUTYRIC ACID; CANNABIS SATIVA SEED OIL; THEANINE; LAVANDULA ANGUSTIFOLIA SUBSP. ANGUSTIFOLIA FLOWER; MAGNESIUM CHLORIDE; MELATONIN; PASSIFLORA INCARNATA FLOWER; POLYSORBATE 80; .ALPHA.-TOCOPHEROL ACETATE; CURCUMIN

Drug Facts

Active Ingredient

Menthol unspecified 6%

Purpose

Topical Analgesic

Uses

For the temporary relief of minor aches and pains of muscles and joints associated with:

- Simple backache
- Muscle strains
- Arthritis
- Bruises
- Sprains

Warnings

For external use only

When using this product

- use only as directed
- consult your doctor before use if using any medications or supplements that contain any of these same ingredients
- do not bandage tightly
- do not use with heating pad
- avoid contact with eyes and mucous membranes
- do not apply to wounds, damaged, broken or irritated skin
- do not use at the same time as other topical analgesics

Stop use and ask a doctor if

- condition worsens
- redness persists, spreads or becomes tender
- symptoms last more than 7 days or clear up and occur again within a few days
- you experience burning swelling or blistering where applied

PREGNANCY OR BREAST FEEDING

If pregnant or breast-feeding, ask a healthcare professional before use.

Keep out of reach of children. If swallowed, get medical help or contact a Poison Control Center right away.

Directions

Adults over 18 years:

- clean and dry affected area
- trim excessive hair for better adhesion
- open pouch and remove patch
- remove backing from patch by grasping both ends and pulling backing apart
- peel off one half of backing and place patch onto affected area
- peel off other half of backing and press and smooth onto skin
- use patch as needed for up to 8 hours. Do not remove when wet or directly after showering or bathing. Allow patch to dry and then slowly remove.
- use one patch at a time for up to 8 hours

Children under 18 years: consult a doctor

Inactive Ingredients

Acrylic adhesive, arnica montana flower extract, chamomile, d-limonene, dipropylene glycol, gamma-aminobutyric acid (GABA), hemp oil, l-theanine, lavender, magnesium chloride, melatonin, passionflower, polysorbate 80, tocopheryl acetate (Vitamin E), white curcumin

Questions

Call 855-438-3944

Other Information

Store in a cool, dry place at room temperature